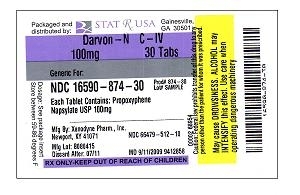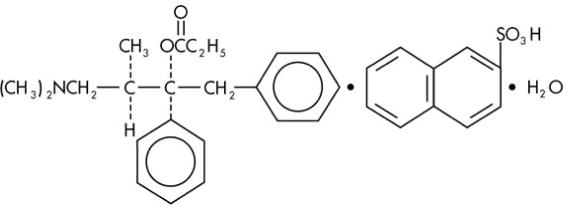 DRUG LABEL: Darvon-N
NDC: 16590-874 | Form: TABLET, FILM COATED
Manufacturer: Stat Rx USA
Category: prescription | Type: HUMAN PRESCRIPTION DRUG LABEL
Date: 20091027
DEA Schedule: CIV

ACTIVE INGREDIENTS: propoxyphene napsylate 100 mg/1 1

DARVON-N - propoxyphene napsylate tablet, film coated

DESCRIPTION

Darvon-N contains propoxyphene napsylate, USP which is an odorless, white crystalline powder with a bitter taste. It is very slightly soluble in water and soluble in methanol, ethanol, chloroform, and acetone. Chemically, it is (αS,1R)-α-[2-(Dimethylamino)-1-methylethyl]-α-phenylphenethyl propionate compound with 2-naphthalenesulfonic acid (1:1) monohydrate, which can be represented by the accompanying structural formula. Its molecular weight is 565.72

Propoxyphene napsylate differs from propoxyphene hydrochloride in that it allows more stable liquid dosage forms and tablet formulations. Because of differences in molecular weight, a dose of 100 mg (176.8 μmol) of propoxyphene napsylate is required to supply an amount of propoxyphene equivalent to that present in 65 mg (172.9 μmol) of propoxyphene hydrochloride.

Each tablet of Darvon-N contains 100 mg (176.8 μmol) propoxyphene napsylate. The tablet also contains cellulose, cornstarch, iron oxides, lactose, magnesium stearate, silicon dioxide, stearic acid, and titanium dioxide.

CLINICAL PHARMACOLOGY Pharmacology

Propoxyphene is a centrally acting opiate analgesic. In vitro studies demonstrated propoxyphene and the metabolite norpropoxyphene inhibit sodium channels (local anesthetic effect) with norpropoxyphene being approximately 2-fold more potent than propoxyphene and propoxyphene approximately 10-fold more potent than lidocaine. Propoxyphene and norpropoxyphene inhibit the voltage-gated potassium current carried by cardiac rapidly activating delayed rectifier (hERG) channels with approximately equal potency. It is unclear if the effects on ion channels occur within therapeutic dose range.

Pharmacokinetics Absorption

Peak plasma concentrations of propoxyphene are reached in 2 to 2.5 h. After a 65-mg oral dose of propoxyphene hydrochloride, peak plasma levels of 0.05 to 0.1 μg/mL for propoxyphene and 0.1 to 0.2 μg/mL for norpropoxyphene (major metabolite) are achieved. Repeated doses of propoxyphene at 6 h intervals lead to increasing plasma concentrations, with a plateau after the ninth dose at 48 h. Propoxyphene has a half-life of 6 to 12 h, whereas that of norpropoxyphene is 30 to 36 h.

Distribution

Propoxyphene is about 80% bound to proteins and has a large volume of distribution, 16 L/kg.

Metabolism

Propoxyphene undergoes extensive first-pass metabolism by intestinal and hepatic enzymes. The major route of metabolism is cytochrome CYP3A4 mediated N-demethylation to norpropoxyphene, which is excreted by the kidneys. Ring hydroxylation and glucuronide formation are minor metabolic pathways.

Excretion

In 48 h, approximately 20 to 25% of the administered dose of propoxyphene is excreted via the urine, most of which is free or conjugated norpropoxyphene. The renal clearance rate of propoxyphene is 2.6 L/min.

SPECIAL POPULATIONS Geriatric Patients

After oral administration of propoxyphene in elderly patients (70-78 years), much longer half-lives of propoxyphene and norpropoxyphene have been reported (propropoxyphene 13 to 35 h, norpropoxyphene 22 to 41 h). In addition, the AUC was an average of 3-fold higher and the Cmax was an average of 2.5-fold higher in the elderly when compared to a younger (20-28 years) population. Longer dosage intervals may be considered in the elderly because the metabolism of propoxyphene may be reduced in this patient population. After multiple oral doses of propoxyphene in elderly patients (70-78 years), the Cmax of the metabolite (norpropoxyphene) was increased 5-fold.

Pediatric Patients

Propoxyphene has not been studied in pediatric patients.

Hepatic Impairment

No formal pharmacokinetic study of propoxyphene has been conducted in patients with mild, moderate or severe hepatic impairment.

After oral administration of propoxyphene in patients with cirrhosis, plasma concentrations of propoxyphene were considerably higher and norpropoxyphene concentrations were much lower than in control patients. This is presumably because of a decreased first-pass metabolism of orally administered propoxyphene in these patients. The AUC ratio of norpropoxyphene: propoxyphene was significantly lower in patients with cirrhosis (0.5 to 0.9) than in controls (2.5 to 4).

Renal Impairment

No formal pharmacokinetic study of propoxyphene has been conducted in patients with mild, moderate or severe renal impairment.

After oral administration of propoxyphene in anephric patients, the AUC and Cmax values were an average of 76% and 88% greater, respectively. Dialysis removes only insignificant amounts (8%) of administered dose of propoxyphene.

Drug Interactions

The metabolism of propoxyphene may be altered by strong CYP3A4 inhibitors (such as ritonavir, ketoconazole, itraconazole, troleandomycin, clarithromycin, nelfinavir, nefazadone, amiodarone, amprenavir, aprepitant, diltiazem, erythromycin, fluconazole, fosamprenavir, grapefruit juice, and verapamil) leading to enhanced propoxyphene plasma levels. On the other hand, strong CYP3A4 inducers such as rifampin may lead to enhanced metabolite (norpropoxyphene) levels.

Propoxyphene is also thought to possess CYP3A4 and CYP2D6 enzyme inhibiting properties. Coadministration with a drug that is a substrate of CYP3A4 or CYP2D6, may result in higher plasma concentrations and increased pharmacologic or adverse effects of that drug.

INDICATIONS AND USAGE

INDICATION

Darvon-N is indicated for the relief of mild to moderate pain.

CONTRAINDICATIONS

Darvon-N is contraindicated in patients with known hypersensitivity to propoxyphene.

Darvon-N is contraindicated in patients with significant respiratory depression (in unmonitored settings or the absence of resuscitative equipment) and patients with acute or severe asthma or hypercarbia.

Darvon-N is contraindicated in any patient who has or is suspected of having paralytic ileus.

WARNINGS Risk of Overdose

There have been numerous cases of accidental and intentional overdose with propoxyphene products either alone or in combination with other CNS depressants, including alcohol. Fatalities within the first hour of overdosage are not uncommon. Many of the propoxyphene-related deaths have occurred in patients with previous histories of emotional disturbances or suicidal ideation/attempts and/or concomitant administration of sedatives, tranquilizers, muscle relaxants, antidepressants, or other CNS-depressant drugs. Do not prescribe propoxyphene for patients who are suicidal or have a history of suicidal ideation.

Respiratory Depression

Respiratory depression is the chief hazard from all opioid agonist preparations. Respiratory depression occurs most frequently in elderly or debilitated patients, usually following large initial doses in non-tolerant patients, or when opioids are given in conjunction with other agents that depress respiration. Darvon-N should be used with extreme caution in patients with significant chronic obstructive pulmonary disease or cor pulmonale, and in patients having substantially decreased respiratory reserve, hypoxia, hypercapnia, or pre-existing respiratory depression. In such patients, even usual therapeutic doses of Darvon-N may decrease respiratory drive to the point of apnea. In these patients alternative non-opioid analgesics should be considered, and opioids should be employed only under careful medical supervision at the lowest effective dose.

Hypotensive Effect

Darvon-N, like all opioid analgesics, may cause severe hypotension in an individual whose ability to maintain blood pressure has been compromised by a depleted blood volume, or after concurrent administration with drugs such as phenothiazines or other agents which compromise vasomotor tone. Darvon-N may produce orthostatic hypotension in ambulatory patients. Darvon-N, like all opioid analgesics, should be administered with caution to patients in circulatory shock, since vasodilatation produced by the drug may further reduce cardiac output and blood pressure.

Head Injury and Increased Intracranial Pressure

The respiratory depressant effects of narcotics and their capacity to elevate cerebrospinal fluid pressure may be markedly exaggerated in the presence of head injury, other intracranial lesions or a pre-existing increase in intracranial pressure. Furthermore, narcotics produce adverse reactions which may obscure the clinical course of patients with head injuries.

Drug Interactions

The concomitant use of propoxyphene and CNS depressants, including alcohol, can result in potentially serious adverse events including death. Because of its added depressant effects, propoxyphene should be prescribed with caution for those patients whose medical condition requires the concomitant administration of sedatives, tranquilizers, muscle relaxants, antidepressants, or other CNS-depressant drugs.

Usage in Ambulatory Patients

Propoxyphene may impair the mental and/or physical abilities required for the performance of potentially hazardous tasks, such as driving a car or operating machinery. The patient should be cautioned accordingly.

Use with Alcohol

Patients should be cautioned about the concomitant use of propoxyphene products and alcohol because of potentially serious CNS-additive effects of these agents that can lead to death.

BOXED WARNING

WARNINGS

There have been numerous cases of accidental and intentional overdose with propoxyphene products either alone or in combination with other CNS depressants, including alcohol. Fatalities within the first hour of overdosage are not uncommon. Many of the propoxyphene-related deaths have occurred in patients with previous histories of emotional disturbance or suicidal ideation/attempts and /or concomitant administration of sedatives, tranquilizers, muscle relaxants, antidepressants, or other CNS-depressant drugs. Do not prescribe propoxyphene for patients who are suicidal or have a history of suicidal ideation.

The metabolism of propoxyphene may be altered by strong CYP3A4 inhibitors (such as ritonavir, ketoconazole, itraconazole, troleandomycin, clarithromycin, nelfinavir, nefazadone, amiodarone, amprenavir, aprepitant, diltiazem, erthromycin, fulconazole, fosamprenavir, grapefruit juice, and verapamil) leading to enhanced propoxyphene plasma levels. Patients receiving propoxyphene and any CYP3A4 inhibitor should be carefully monitored for an extended period of time and dosage adjustments should be made if warranted (see Clinical Pharmacology - Drug Interactions, Warnings, Precautions and Dosage and Administration for further information.)

PRECAUTIONS Tolerance and Physical Dependence

Tolerance is the need for increasing doses of opioids to maintain a defined effect such as analgesia (in the absence of disease progression or other external factors). Physical dependence is manifested by withdrawal symptoms after abrupt discontinuation of a drug or upon administration of an antagonist. Physical dependence and tolerance are not unusual during chronic opioid therapy.

The opioid abstinence or withdrawal syndrome is characterized by some or all of the following: restlessness, lacrimation, rhinorrhea, yawning, perspiration, chills, myalgia, and mydriasis. Other symptoms also may develop, including: irritability, anxiety, backache, joint pain, weakness, abdominal cramps, insomnia, nausea, anorexia, vomiting, diarrhea, or increased blood pressure, respiratory rate, or heart rate. In general, opioids should not be abruptly discontinued (see Dosage and Administration: Cessation of Therapy).

If Darvon-N is abruptly discontinued in a physically dependent patient, an abstinence syndrome may occur (see Drug Abuse and Dependance). If signs and symptoms of withdrawal occur, patients should be treated by reinstitution of opioid therapy followed by gradual tapered dose reduction of Darvon-N combined with symptomatic support (see Dosage and Administration: Cessation of Therapy).

Use in Pancreatic/Biliary Tract Disease

Darvon-N may cause spasm of the sphincter of Oddi and should be used with caution in patients with biliary tract disease, including acute pancreatitis. Opioids like Darvon-N may cause increases in the serum amylase level.

Hepatic or Renal Impairment

Insufficient information exists to make appropriate dosing recommendations regarding the use of either propoxyphene in patients with hepatic or renal impairment as a function of degree of impairment. Higher plasma concentrations and/or delayed elimination may occur in case of impaired hepatic function and/or impaired renal function (see Clinical Pharmacology). If the drug is used in these patients, it should be used with caution because of the hepatic metabolism and renal excretion of propoxyphene metabolites.

Information for Patients/Caregivers

1. Patients should be advised to report pain and adverse experiences occurring during therapy. Individualization of dosage is essential to make optimal use of this medication.
2. Patients should be advised not to adjust the dose of Darvon-N without consulting the prescribing professional.
3. Patients should be advised that Darvon-N may impair mental and/or physical ability required for the performance of potentially hazardous tasks (e.g., driving, operating heavy machinery).
4. Patients should not combine Darvon-N with central nervous system depressants (e.g., sleep aids, tranquilizers) except by the orders of the prescribing physician, because additive effects may occur.
5. Patients should be instructed not to consume alcoholic beverages, including prescription and over-the-counter medications that contain alcohol, while using Darvon-N because of risk of serious adverse events including death.
6. Women of childbearing potential who become, or are planning to become, pregnant should be advised to consult their physician regarding the effects of analgesics and other drug use during pregnancy on themselves and their unborn child.
7. Patients should be advised that Darvon-N is a potential drug of abuse. They should protect it from theft, and it should never be given to anyone other than the individual for whom it was prescribed.
8. Patients should be advised that if they have been receiving treatment with Darvon-N for more than a few weeks and cessation of therapy is indicated, it may be appropriate to taper the Darvon-N dose, rather than abruptly discontinue it, due to the risk of precipitating withdrawal symptoms. Their physician can provide a dose schedule to accomplish a gradual discontinuation of the medication.

Drug Interactions with Propoxyphene

Propoxyphene is metabolized mainly via the human cytochrome P450 3A4 isoenzyme system (CYP3A4), therefore potential interactions may occur when propoxyphene is administered concurrently with agents that affect CYP3A4 activity.

The metabolism of propoxyphene may be altered by strong CYP3A4 inhibitors (such as ritonavir, ketoconazole, itraconazole, troleandomycin, clarithromycin, nelfinavir, nefazadone, amiodarone, amprenavir, aprepitant, diltiazem, erythromycin, fluconazole, fosamprenavir, grapefruit juice, and verapamil) leading to enhanced propoxyphene plasma levels. Coadministration with agents that induce CYP3A4 activity may reduce the efficacy of propoxyphene. Strong CYP3A4 inducers such as rifampin may lead to enhanced metabolite (norpropoxyphene) levels.

Propoxyphene is also thought to possess CYP3A4 and CYP2D6 enzyme inhibiting properties and coadministration with drugs that rely on either of these enzymes for metabolism may result in increased pharmacologic or adverse effects of that drug. Severe neurologic signs, including coma, have occurred with concurrent use of carbamazepine (metabolized by CYP3A4).

Increased risk of bleeding has been observed with warfarin-like agents when given along with propoxyphene; however, the mechanistic basis of this interaction is unknown.

CNS Depressants

Patients receiving narcotic analgesics, general anesthetics, phenothiazines, other tranquilizers, sedative-hypnotics or other CNS depressants (including alcohol) concomitantly with propoxyphene may exhibit an additive CNS depression. Interactive effects resulting in respiratory depression, hypotension, profound sedation, or coma may result if these drugs are taken in combination with the usual dosage of Darvon-N. When such combined therapy is contemplated, the dose of one or both agents should be reduced.

Mixed Agonist/Antagonist Opioid Analgesics

Agonist/antagonist analgesics (i.e., pentazocine, nalbuphine, butorphanol and buprenorphine) should be administered with caution to patients who have received or are receiving a course of therapy with a pure opioid agonist analgesic such as Darvon-N. In this situation, mixed agonist/antagonist analgesics may reduce the analgesic effect of Darvon-N and/or may precipitate withdrawal symptoms in these patients.

Monoamine Oxidase Inhibitors (MAOIs)

MAOIs have been reported to intensify the effects of at least one opioid drug causing anxiety, confusion and significant depression of respiration or coma. The use of Darvon-N is not recommended for patients taking MAOIs or within 14 days of stopping such treatment.

Carcinogenesis, Mutagenesis, Impairment of Fertility

The mutagenic and carcinogenic potential of propoxyphene has not been evaluated.

In animal studies there was no effect of propoxyphene on mating behavior, fertility, duration of gestation, or parturition when rats were fed propoxyphene as a component of their daily diet at estimated daily propoxyphene intake up to 8-fold greater than the maximum human equivalent dose (HED) based on body surface area comparison. At this highest dose, fetal weight and survival on postnatal day 4 was reduced.

Pregnancy Risk summary Pregnancy category C.

There are no adequate and well-controlled studies of propoxyphene in pregnant women. While there are limited data in the published literature, adequate animal reproduction studies have not been conducted with propoxyphene. Therefore, it is not known whether propoxyphene can affect reproduction or cause fetal harm when administered to a pregnant woman. Propoxyphene should be given to a pregnant woman only if clearly needed.

Clinical considerations

Propoxyphene and its major metabolite, norpropoxyphene, cross the human placenta. Neonates whose mothers have taken opiates chronically may exhibit respiratory depression or withdrawal symptoms.

Data

In published animal reproduction studies, no teratogenic effects occurred in offspring born to pregnant rats or rabbits that received propoxyphene during organogenesis. Pregnant animals received propoxyphene doses approximately 10-fold (rats) and 4-fold (rabbits) the maximum recommended human dose (based on mg/m^2 body surface area comparison).

Nursing Mothers

Propoxyphene, norpropoxyphene (major metabolite), are excreted in human milk. Published studies of nursing mothers using propoxyphene detected no adverse effects in nursing infants. Based on a study of six mother-infant pairs, an exclusively breastfed infant receives approximately 2% of the maternal weight-adjusted dose. Norpropoxyphene is renally excreted and renal clearance is lower in neonates than in adults. Therefore, it is possible that prolonged maternal propoxyphene use could result in norpropoxyphene accumulation in a breastfed infant. Watch breastfeeding infants for signs of sedation including poor feeding, somnolence, or respiratory depression. Caution should be exercised when Darvon-N is administered to a nursing woman.

Pediatric Patients

Safety and effectiveness in pediatric patients have not been established.

Elderly Patients

Clinical studies of Darvon-N did not include sufficient numbers of subjects aged 65 and over to determine whether they respond differently from younger subjects. However, postmarketing reports suggest that patients over the age of 65 may be more susceptible to CNS-related side effects. Therefore, dose selection for an elderly patient should be cautious, usually starting at the low end of the dosing range, reflecting the greater frequency of decreased hepatic, renal, or cardiac function, and of concomitant disease or other drug therapy. Decreased total daily dosage should be considered (see Dosage and Administration).

ADVERSE REACTIONS

In hospitalized patients, the most frequently reported were dizziness, sedation, nausea, and vomiting. Other adverse reactions include constipation, abdominal pain, skin rashes, lightheadedness, headache, weakness, euphoria, dysphoria, hallucinations, and minor visual disturbances.

The most frequently reported postmarketing adverse events have included completed suicide, accidental and intentional overdose, drug dependence, cardiac arrest, coma, drug ineffective, drug toxicity, nausea, respiratory arrest, cardio-respiratory arrest, death, vomiting, dizziness, convulsion, confusional state, and diarrhea.

Additional adverse experiences reported through postmarketing surveillance include:

Cardiac disorders: arrhythmia, bradycardia, cardiac/respiratory arrest, congestive arrest, congestive heart failure (CHF), tachycardia, myocardial infarction (MI)

Eye disorder: eye swelling, vision blurred

General disorder and administration site conditions: drug ineffective, drug interaction, drug tolerance, influenza type illness, drug withdrawal syndrome

Gastrointestinal disorder: gastrointestinal bleed, acute pancreatitis

Hepatobiliary disorder: hepatic steatosis, hepatomegaly, hepatocellular injury

Immune system disorder: hypersensitivity

Injury poisoning and procedural complications: drug toxicity, hip fracture, multiple drug overdose, narcotic overdose

Investigations: blood pressure decreased, heart rate elevated/abnormal

Metabolism and nutrition disorder: metabolic acidosis

Nervous system disorder: ataxia, coma, dizziness, somnolence, syncope

Psychiatric: abnormal behavior, confusional state, hallucinations, mental status change

Respiratory, thoracic, and mediastinal disorders: respiratory depression, dyspnoea

Skin and subcutaneous tissue disorder: rash, itch

Liver dysfunction has been reported in association with Darvon-N. Propoxyphene therapy has been associated with abnormal liver function tests and, more rarely, with instances of reversible jaundice (including cholestatic jaundice).

Subacute painful myopathy has been reported following chronic propoxyphene overdosage.

DRUG ABUSE AND DEPENDENCE Controlled Substance

Darvon-N is a Schedule IV narcotic under the U.S. Controlled Substances Act. Darvon-N can produce drug dependence of the morphine type, and therefore, has the potential for being abused. Psychic dependence, physical dependence and tolerance may develop upon repeated administration. Darvon-N should be prescribed and administered with the same degree of caution appropriate to the use of other narcotic-containing medications.

Abuse

Since Darvon-N is a mu-opioid agonist, it may be subject to misuse, abuse, and addiction. Addiction to opioids prescribed for pain management has not been estimated. However, requests for opioids from opioid-addicted patients occur. As such, physicians should take appropriate care in prescribing Darvon-N.

Dependence

Opioid analgesics may cause psychological and physical dependence. Physical dependence results in withdrawal symptoms in patients who abruptly discontinue the drug after long term administration. Also, symptoms of withdrawal may be precipitated through the administration of drugs with mu-opioid antagonist activity, e.g., naloxone or mixed agonist/antagonist analgesics (e.g., pentazocine, butorphanol, nalbuphine, dezocine) (see Overdosage). Physical dependence usually does not occur to a clinically significant degree, until after several weeks of continued opioid usage. Tolerance, in which increasingly larger doses are required to produce the same degree of analgesia, is initially manifested by a shortened duration of an analgesic effect and subsequently, by decreases in the intensity of analgesia.

In chronic pain patients, and in opioid-tolerant cancer patients, the administration of Darvon-N should be guided by the degree of tolerance manifested and the doses needed to adequately relieve pain.

The severity of the Darvon-N abstinence syndrome may depend on the degree of physical dependence. Withdrawal is characterized by rhinitis, myalgia, abdominal cramping, and occasional diarrhea. Most observable symptoms disappear in 5 to 14 days without treatment; however, there may be a phase of secondary or chronic abstinence which may last for 2 to 6 months characterized by insomnia, irritability, and muscular aches. The patient may be detoxified by gradual reduction of the dose. Gastrointestinal disturbances or dehydration should be treated with supportive care.

OVERDOSAGE

Overdose of Darvon-N may present with the signs and symptoms of propoxyphene overdose. Fatalities within the first hour of overdosage are not uncommon.

In all cases of suspected overdosage, call your regional Poison Control Center to obtain the most up-to-date information about the treatment of overdose. This recommendation is made because, in general, information regarding the treatment of overdosage may change more rapidly than do package inserts.

Initial consideration should be given to the management of the CNS effects of propoxyphene overdosage. Resuscitative measures should be initiated promptly.

Symptoms of Propoxyphene Overdosage

The manifestations of acute overdosage with propoxyphene are those of narcotic overdosage. The patient is usually somnolent but may be stuporous or comatose and convulsing. Respiratory depression is characteristic. The ventilatory rate and/or tidal volume is decreased, which results in cyanosis and hypoxia. Pupils, initially pinpoint, may become dilated as hypoxia increases. Cheyne-Stokes respiration and apnea may occur. Blood pressure and heart rate are usually normal initially, but blood pressure falls and cardiac performance deteriorates, which ultimately results in pulmonary edema and circulatory collapse, unless the respiratory depression is corrected and adequate ventilation is restored promptly. Cardiac arrhythmias and conduction delay may be present. A combined respiratory-metabolic acidosis occurs owing to retained CO2 (hypercapnia) and to lactic acid formed during anaerobic glycolysis. Acidosis may be severe if large amounts of salicylates have also been ingested. Death may occur.

Treatment of Propoxyphene Overdosage

Attention should be directed first to establishing a patent airway and to restoring ventilation. Mechanically assisted ventilation, with or without oxygen, may be required, and positive pressure respiration may be desirable if pulmonary edema is present. The opioid antagonist naloxone will markedly reduce the degree of respiratory depression, and should be administered promptly, preferably intravenously. The duration of action of the antagonist may be brief. If no response is observed after 10 mg of naloxone have been administered, the diagnosis of propoxyphene toxicity should be questioned.

In addition to the use of an opioid antagonist, the patient may require careful titration with an anticonvulsant to control convulsions. Activated charcoal can adsorb a significant amount of ingested propoxyphene. Dialysis is of little value in poisoning due to propoxyphene. Efforts should be made to determine whether other agents, such as alcohol, barbiturates, tranquilizers, or other CNS depressants, were also ingested, since these increase CNS depression as well as cause specific toxic effects or death.

DOSAGE AND ADMINISTRATION

Darvon-N is intended for the management of mild to moderate pain. The dose should be individually adjusted according to severity of pain, patient response and patient size.

Darvon-N is given orally. The usual dosage is one 100 mg propoxyphene napsylate tablet every 4 hours as needed for pain. The maximum dose of Darvon-N is 6 tablets per day. Do not exceed the maximum daily dose.

Patients receiving propoxyphene and any CYP3A4 inhibitor should be carefully monitored for an extended period of time and dosage adjustments should be made if warranted.

Consideration should be given to a reduced total daily dosage in elderly patients and in patients with hepatic or renal impairment.

Cessation of Therapy

For patients who used Darvon-N on a regular basis for a period of time, when therapy with Darvon-N is no longer needed for the treatment of their pain, it may be useful to gradually discontinue the Darvon-N over time to prevent the development of an opioid abstinence syndrome (narcotic withdrawal). In general, therapy can be decreased by 25% to 50% per day with careful monitoring for signs and symptoms of withdrawal (see Drug Abuse and Dependence for description of the signs and symptoms of withdrawal). If the patient develops these signs or symptoms, the dose should be raised to the previous level and titrated down more slowly, either by increasing the interval between decreases, decreasing the amount of change in dose, or both.

HOW SUPPLIED

Darvon-N Tablets are available in:

The 100 mg tablets are buff colored, elliptical shaped, film coated, and imprinted with the script “DARVON-N 100” on one side of the tablet, using edible black ink. They are available as follows:

Bottles of 100 | NDC 66479-512-10

Store at 25°C (77°F); excursions are permitted to 15°- 30°C (59°- 86°F) [see USP Controlled Room Temperature].

Inform patients of the availability of a Medication Guide for Darvon/Darvon-N that accompanies each prescription dispensed. Instruct patients to read the Darvon/Darvon-N Medication Guide prior to using Darvon.

Darvon, Darvon-N, Darvocet, and Darvocet-N are registered trademarks of

Xanodyne Pharmaceuticals, Inc.

© 2009 Xanodyne Pharmaceuticals, Inc.

Marketed by:

Xanodyne Pharmaceuticals, Inc.

Newport, KY
41071

PI-512-A
REV. 09-2009

MEDICATION GUIDE

DARVON-N® [dar-von-N] (C-IV)

(propoxyphene napsylate)

Tablets

DARVON® [dar-von](C-IV)

(propoxyphene hydrochloride capsules)

Puvules®

Read this Medication Guide before you start taking Darvon-N or Darvon, and each time you get a refill. There may be new information. This information does not take the place of talking to your doctor about your medical condition or your treatment.

What is the most important information I should know about Darvon-N and Darvon?

Darvon-N and Darvon, and other medicines that contain propoxyphene can cause serious side effects, including:

Overdoses by accident or on purpose (intentional overdose). Overdoses with Darvon-N and Darvon may happen when it is taken by itself, or with alcohol or other medicines that can also decrease your breathing and make you very sleepy.

- Death can happen within 1 hour of taking an overdose of Darvon-N or Darvon.
  Many of the deaths that happen in people who take Darvon-N and Darvon happen in those who:
  - have emotional problems
  - have thoughts of suicide or attempted suicide, or
  - also take antidepressants, sedatives, tranquilizers, muscle relaxants, or other medicines that affect your breathing and make you very sleepy. You should not use any of these medicines with Darvon-N or Darvon without talking to your doctor.
- Before taking Darvon-N or Darvon tell your doctor if you:
  - have a lung problem, such as COPD or cor pulmonale
  - have liver or kidney problems
  - have problems with your pancreas or gallbladder
  - have a history of head injury
  - are over age 65
  - have a history of drug or alcohol abuse or addiction

Take Darvon-N and Darvon exactly as prescribed. Do not change your dose or stop taking Darvon-N or Darvon without first talking to your doctor.

- If you take Darvon-N, do not take more than 6 tablets in one day.
- If you take Darvon, do not take more than 6 capsules in one day.

- Before taking Darvon-N or Darvon, tell your doctor about all the medicines you take. Darvon-N or Darvon and many other medicines may interact with each other and may cause serious side effects. Certain medicines can affect how your liver breaks down other medicines. See “What should I tell my doctor before taking Darvon-N or Darvon?”
- Do not drink grapefruit juice or eat grapefruit while you take Darvon-N or Darvon. Grapefruit juice may interact with Darvon-N or Darvon.

- Do not drink alcohol while using Darvon-N or Darvon. Using alcohol with Darvon-N or Darvon may increase your risk of having dangerous side effects.

What are Darvon-N and Darvon?

- Darvon-N and Darvon are prescription medicines used to treat mild to moderate pain.

- Darvon-N and Darvon are federally controlled substances (C-IV) because they are strong opioid pain medicines that can be abused by people who abuse prescription medicines or street drugs.
- Prevent theft, misuse or abuse. Keep Darvon-N or Darvon in a safe place to protect it from being stolen. Darvon-N and Darvon can be a target for people who misuse or abuse prescription medicines or street drugs.
- Never give Darvon-N or Darvon to anyone else, even if they have the same symptoms that you have. It may harm them or even cause death. Selling or giving away this medicine is against the law.

It is not known if Darvon-N and Darvon are safe and effective in children younger than age 18.

Who should not take Darvon-N or Darvon?

Do not take Darvon-N or Darvon if you:

- are allergic to propoxyphene. Ask your doctor if you are not sure. See the end of this Medication Guide for a list of the ingredients in Darvon-N and Darvon.
- are having an asthma attack or have severe asthma, trouble breathing, or have a lung problem
- have a bowel blockage called paralytic ileus

What should I tell my doctor before taking Darvon-N or Darvon?

Before you take Darvon-N or Darvon, tell your doctor:

- if you have any of the conditions listed in the section “What is the most important information I should know about Darvon-N and Darvon?”
- if you are allergic to propoxyphene
- if you plan to have surgery with general anesthesia
- if you are pregnant or plan to become pregnant.
- if you take Darvon-N or Darvon regularly before your baby is born, your newborn baby may have withdrawal symptoms because their body has become used to the medicine. Symptoms of withdrawal in a newborn baby may include:

- irritability
- crying more than usual)
- shaking (tremors
- jitteriness
- breathing faster than normal

- diarrhea or more stools than normal
- vomiting
- fever

- if you take Darvon-N or Darvon right before your baby is born, your baby could have breathing problems.
- if you are breast-feeding or plan to breast-feed. Some Darvon-N or Darvon passes into breast milk.

Tell your doctor about all the medicines you take, including prescription, and non-prescription medicines, vitamins, and herbal supplements. Darvon-N and Darvon interacts with many medicines and may lead to serious side effects. The doses of certain medicines may need to be changed.

Especially tell your doctor if you take:

See “What is the most important information I should know about Darvon-N and Darvon?”

- certain medicines that can affect how your liver breaks down other medicines
- a monoamine oxidase inhibitor (MAOI) medicine
- other medicines that make you sleepy, such as: other medicines for pain, including other opioid medicines, anti-depressant medicines, sleeping pills, anti-anxiety medicines, muscle relaxants, anti-nausea medicines, or tranquilizers
- a blood pressure medicine
- a blood-thinner medicine. You may have an increased risk of bleeding while also taking Darvon-N or Darvon.

Ask your doctor or pharmacist if you are not sure if your medicine is one listed above.

Know the medicines you take. Keep a list of them to show to your doctor and pharmacist when you get a new medicine.

How should I take Darvon-N or Darvon?

See “What is the most important information I should know about Darvon-N and Darvon?”

- Take Darvon-N or Darvon exactly as prescribed.
- If you take too much Darvon-N or Darvon, or take it with alcohol or other medicines, you may overdose. See “What is the most important information I should know about Darvon-N or Darvon?” You will need medical help right away if you think you have taken an overdose of Darvon-N or Darvon. A large overdose could cause you to become unconscious and die.

Signs and symptoms of an overdose of Darvon-N or Darvon include:

- you are very sleepy or do not respond to others
- confusion
- have trouble breathing or stop breathing
- changes in blood pressure and heart rate

What are the possible side effects of Darvon-N and Darvon?

Darvon-N and Darvon can cause serious side effects, including:

See “What is the most important information I should know about Darvon-N and Darvon?”

- Serious breathing problems that can become life-threatening. This is especially true if you already have a serious lung or breathing problem, or your body is not used to opioid pain medicines. This can happen even if you take Darvon-N or Darvon exactly as prescribed by your doctor. Call your doctor or get medical help right away if:
  - your breathing slows down
  - you have shallow breathing (little chest movement with breathing)
  - you feel faint, dizzy, confused, or
  - you have any other unusual symptoms
- Darvon-N and Darvon can cause your blood pressure to drop. This can make you feel dizzy and faint if you get up too fast from sitting or lying down. Low blood pressure is also more likely to happen if you take other medicines that can also lower your blood pressure. Severe low blood pressure can happen if you lose blood or take certain other medicines.
- Sleepiness. Darvon-N and Darvon can cause sleepiness and may affect your ability to make decisions, think clearly, or react quickly. Do not drive, operate heavy machinery, or do other dangerous activities until you know how Darvon-N or Darvon affects you.
- Darvon-N and Darvon can cause physical dependence if you take it for more than a few weeks. Do not stop taking Darvon-N or Darvon all of a sudden. You could become sick with uncomfortable withdrawal symptoms (for example, nausea, vomiting, diarrhea, anxiety, and shivering) because your body has become used to the medicine. Physical dependence is not the same as drug addiction. Your doctor can tell you more about the differences between physical dependence and drug addiction.

Tell your doctor if you have any of these withdrawal symptoms while you slowly stop taking Darvon-N or Darvon. You may need to stop Darvon-N or Darvon more slowly.

Common side effects of Darvon-N and Darvon include:

- dizziness
- feeling sleepy
- nausea and vomiting
- constipation
- stomach area (abdominal) pain
- skin rashes
- lightheadedness
- headache
- weakness
- feeling of excitement (elation) or discomfort

- seeing, hearing, or sensing things that are not really there (hallucinations)
- blurred vision

Call your doctor for medical advice about side effects. You may report side effects to FDA at 1-800-FDA-1088.

You may also report side effects to Xanodyne Pharmaceuticals, Inc. at 1-877-773-7793.

How should I store Darvon-N and Darvon?

- Store Darvon-N between 59°F to 86°F (15°C to 30°C).
- Store Darvon between 68°F to 77°F (20°C to 25°C).

Keep Darvon-N, Darvon and all medicines out of the reach of children.

General information about Darvon-N and Darvon

Medicines are sometimes prescribed for purposes other than those listed in a Medication Guide. Do not use Darvon-N or Darvon for a purpose for which it was not prescribed. Do not give Darvon-N or Darvon to others even if they have the same symptoms you have. It may harm them and is against the law.

This Medication Guide summarizes the most important information about Darvon-N and Darvon. If you would like more information, talk with your doctor. You can ask your pharmacist or doctor for information about Darvon-N and Darvon that is written for health professionals. For more information, go to www.Xanodyne.com or call 1-877-773-7793.

What are the ingredients in Darvon-N and Darvon?

Darvon-N:

Active ingredient: propoxyphene napsylate

Inactive ingredients: cellulose, cornstarch, iron oxides, lactose, magnesium stearate, silicon dioxide, stearic acid, and titanium dioxide

Darvon:

Active ingredient: propoxyphene hydrochloride

Inactive ingredients: D and C Red No. 33, FD and C Yellow No. 6, gelatin, magnesium stearate, silicone, starch, titanium dioxide, and other inactive ingredients

Xanodyne Pharmaceuticals, Inc.
Newport, KY 41071

Issued 09/2009

This Medication Guide has been approved by the U.S. Food and Drug Administration.

Darvon, Darvon-N, Darvocet-N and Darvocet are registered trademarks of Xanodyne Pharmaceuticals, Inc.

© 2009 Xanodyne Pharmaceuticals, Inc.

Marketed by:

Xanodyne Pharmaceuticals, Inc.

MG-510/512-A
Rev. 09/2009

Revised: 09/2009 Xanodyne Pharmaceuticals, Inc.

PRODUCT LABEL